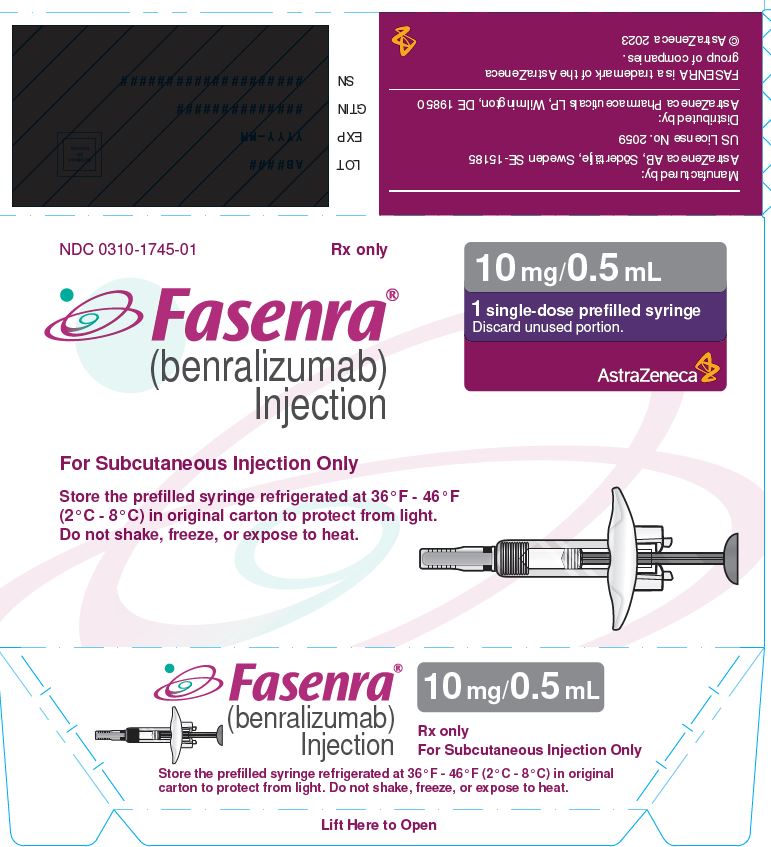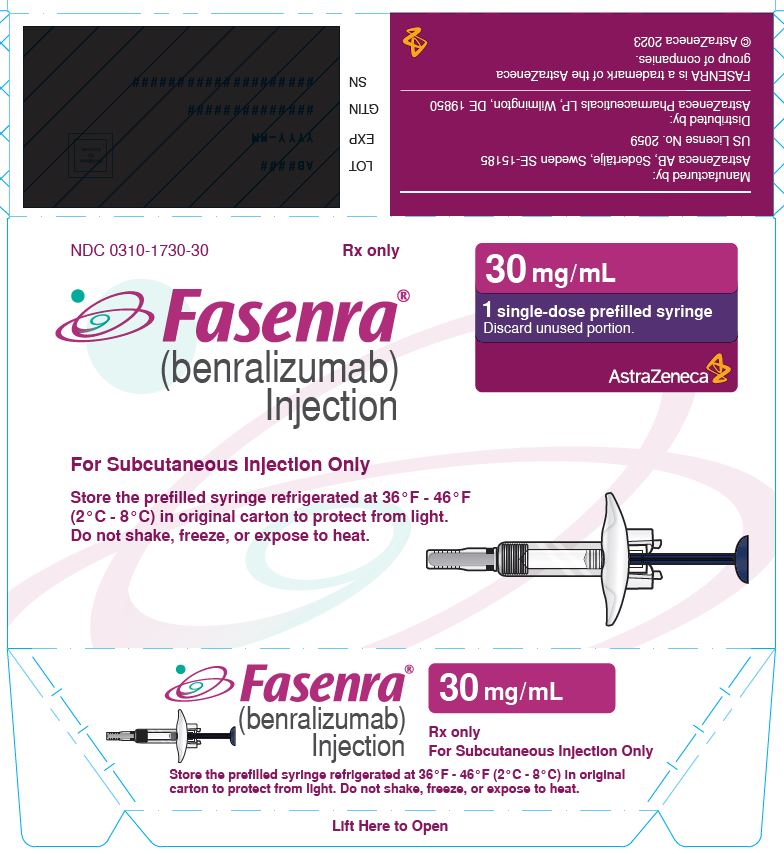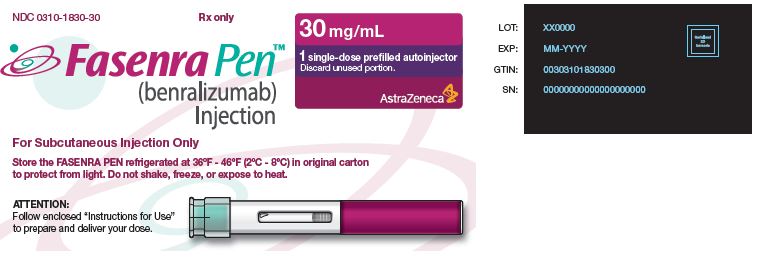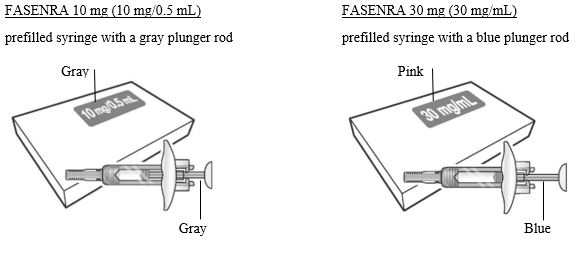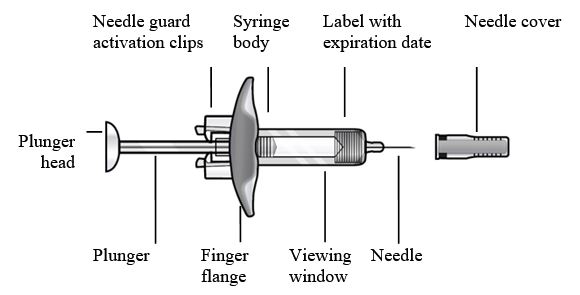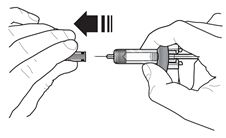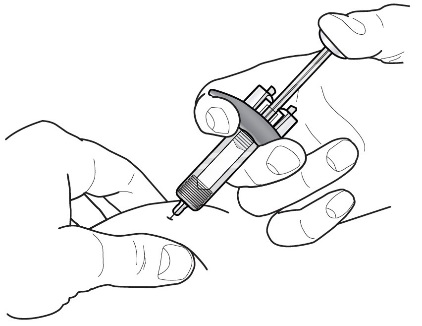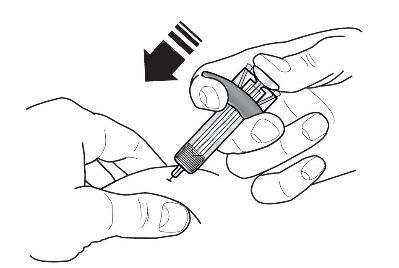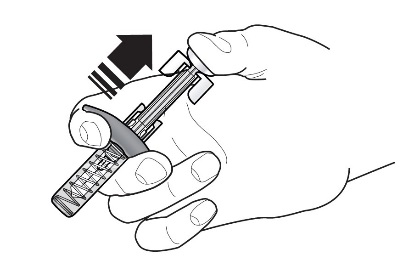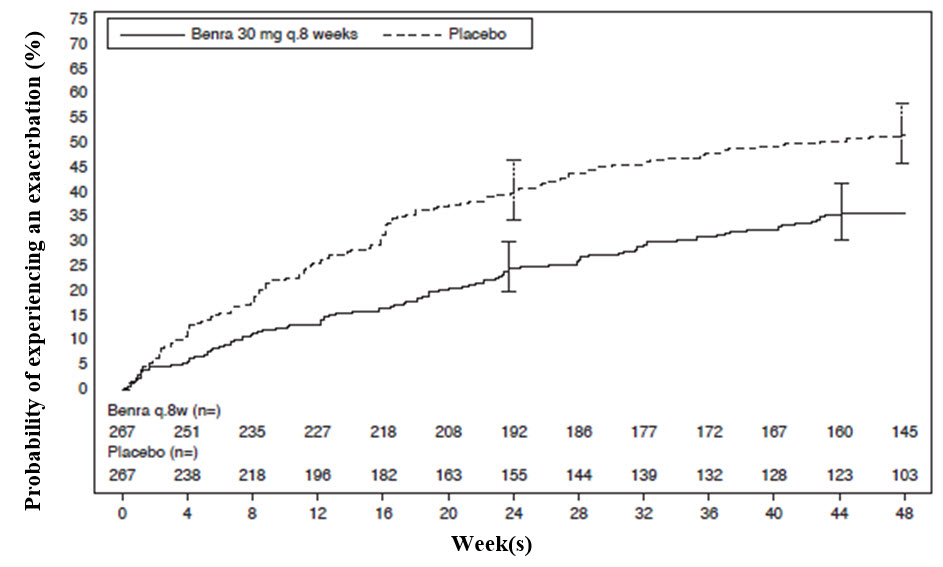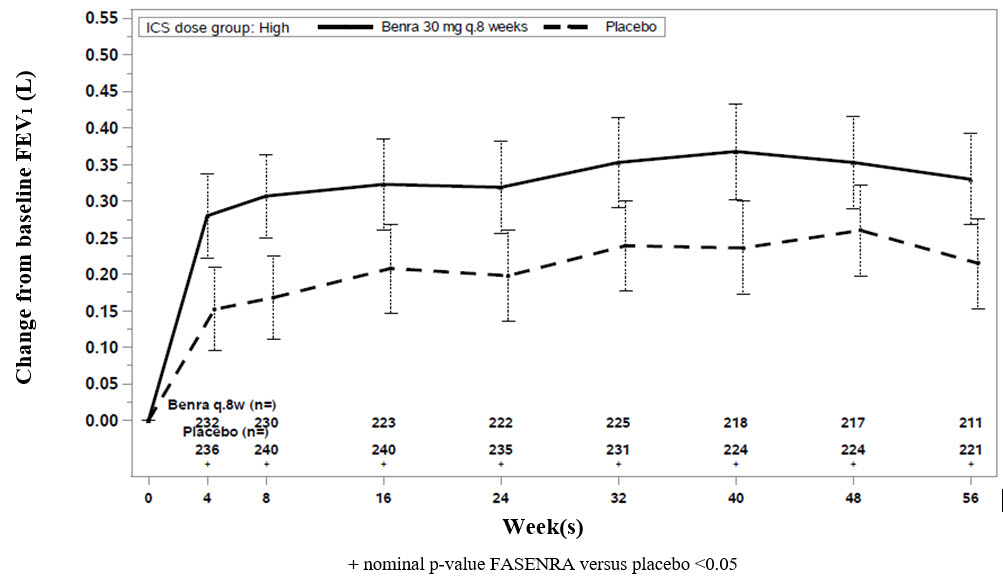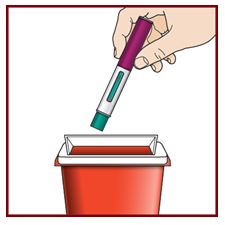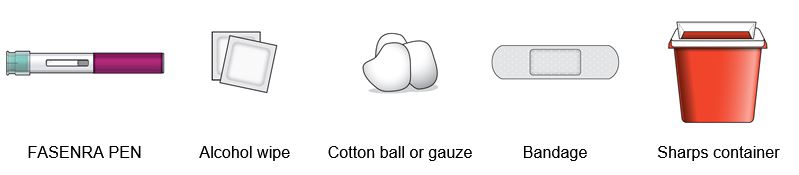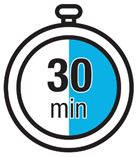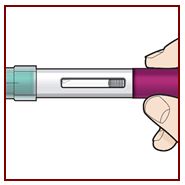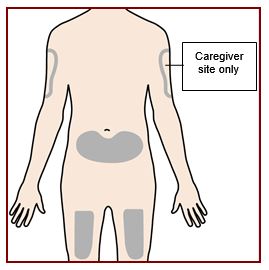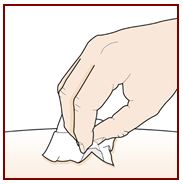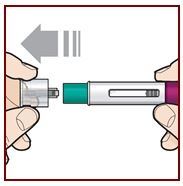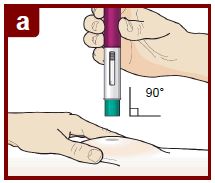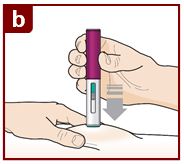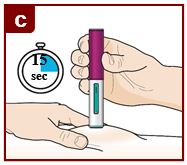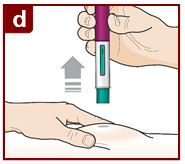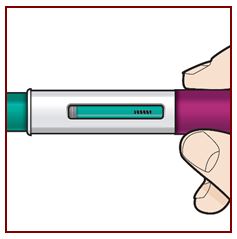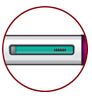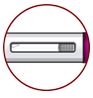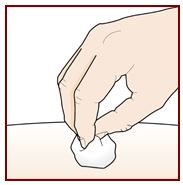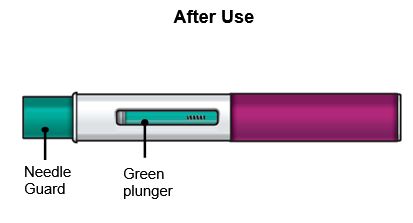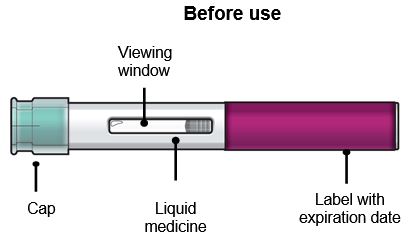 DRUG LABEL: FASENRA
NDC: 0310-1730 | Form: INJECTION, SOLUTION
Manufacturer: AstraZeneca Pharmaceuticals LP
Category: prescription | Type: HUMAN PRESCRIPTION DRUG LABEL
Date: 20240917

ACTIVE INGREDIENTS: BENRALIZUMAB 30 mg/1 mL
INACTIVE INGREDIENTS: HISTIDINE 1.4 mg/1 mL; HISTIDINE MONOHYDROCHLORIDE 2.3 mg/1 mL; POLYSORBATE 20 0.06 mg/1 mL; TREHALOSE DIHYDRATE 95 mg/1 mL; WATER 910 mg/1 mL

HIGHLIGHTS OF PRESCRIBING INFORMATION

These highlights do not include all the information needed to use FASENRA® safely and effectively. See full prescribing information for FASENRA.
FASENRA (benralizumab) injection, for subcutaneous use
Initial U.S. Approval: 2017

RECENT MAJOR CHANGES

Indications and Usage (1) 09/2024

Dosage and Administration (2.1, 2.3, 2.4) 04/2024

Dosage and Administration, EGPA (2.2) 09/2024

1 INDICATIONS AND USAGE

FASENRA is an interleukin-5 receptor alpha-directed cytolytic monoclonal antibody (IgG1, kappa) indicated for:

- add-on maintenance treatment of adult and pediatric patients aged 6 years and older with severe asthma, and with an eosinophilic phenotype. (1.1)
- treatment of adult patients with eosinophilic granulomatosis with polyangiitis (EGPA). (1.2)

Limitations of Use:

Not for relief of acute bronchospasm or status asthmaticus. (1.1)

2 DOSAGE AND ADMINISTRATION

Administer by subcutaneous injection. (2.3)

Asthma

Adult and Adolescent Patients 12 Years of Age and Older:

- Recommended dosage is 30 mg every 4 weeks for first 3 doses followed by once every 8 weeks thereafter. (2.1)

Pediatric Patients 6 Years to 11 Years of Age:

- Weighing Less Than 35 kg: the recommended dosage is 10 mg every 4 weeks for first 3 doses followed by once every 8 weeks thereafter. (2.1)
- Weighing 35 kg or More: the recommended dosage is 30 mg every 4 weeks for first 3 doses followed by once every 8 weeks thereafter. (2.1)

EGPA

Recommended dosage is 30 mg every 4 weeks. (2.2)

See full prescribing information for administration instructions of FASENRA prefilled syringe and FASENRA PEN. (2.4, 2.5)

3 DOSAGE FORMS AND STRENGTHS

Injection:

- 10 mg/0.5 mL solution in a single-dose prefilled syringe. (3)
- 30 mg/mL solution in a single-dose prefilled syringe. (3)
- 30 mg/mL solution in a single-dose autoinjector FASENRA PEN. (3)

4 CONTRAINDICATIONS

Known hypersensitivity to benralizumab or excipients. (4)

5 WARNINGS AND PRECAUTIONS

- Hypersensitivity reactions: Hypersensitivity reactions (e.g., anaphylaxis, angioedema, urticaria, rash) have occurred after administration of FASENRA. Discontinue in the event of a hypersensitivity reaction. (5.1)
- Reduction in Corticosteroid Dosage: Do not discontinue systemic or inhaled corticosteroids abruptly upon initiation of therapy with FASENRA. Decrease corticosteroids gradually, if appropriate. (5.3)
- Parasitic (Helminth) Infection: Treat patients with pre-existing helminth infections before therapy with FASENRA. If patients become infected while receiving FASENRA and do not respond to anti-helminth treatment, discontinue FASENRA until the parasitic infection resolves. (5.4)

6 ADVERSE REACTIONS

Most common adverse reactions (incidence greater than or equal to 5%) include headache and pharyngitis. (6.1, 6.2)

To report SUSPECTED ADVERSE REACTIONS, contact AstraZeneca at 1-800-236-9933 or FDA at 1-800-FDA-1088 or www.fda.gov/medwatch.

FULL PRESCRIBING INFORMATION

1 INDICATIONS AND USAGE

1.1 Asthma

FASENRA is indicated for the add-on maintenance treatment of adult and pediatric patients aged 6 years and older with severe asthma, and with an eosinophilic phenotype [see Use in Specific Populations (8.4), Clinical Studies (14.1)].

Limitations of Use:

- FASENRA is not indicated for the relief of acute bronchospasm or status asthmaticus.

1.2 Eosinophilic Granulomatosis with Polyangiitis

FASENRA is indicated for the treatment of adult patients with eosinophilic granulomatosis with polyangiitis (EGPA).

2 DOSAGE AND ADMINISTRATION

2.1 Recommended Dosage for Asthma

Adult and Adolescent Patients 12 Years of Age and Older

The recommended dosage of FASENRA is 30 mg (one injection) administered subcutaneously every 4 weeks for the first 3 doses, and then every 8 weeks thereafter.

Pediatric Patients 6 to 11 Years of Age

The recommended dosage of FASENRA for pediatric patients 6 to 11 years of age is based on body weight as provided in Table 1.

Table 1. Recommended Dosage of FASENRA in Pediatric Patients 6 to 11 Years of Age with Asthma
Body weight | Recommended Dosage
Less than 35 kg | 10 mg (one injection) administered subcutaneously every 4 weeks for the first 3 doses, and then every 8 weeks thereafter.
35 kg or more | 30 mg (one injection) administered subcutaneously every 4 weeks for the first 3 doses, and then every 8 weeks thereafter.

2.2 Recommended Dosage for EGPA

The recommended dosage of FASENRA is 30 mg (one injection) administered once every 4 weeks by subcutaneous injection.

2.3 General Administration Instructions

FASENRA is for subcutaneous use only.

FASENRA is intended for use under the guidance of a healthcare provider. In line with clinical practice, monitoring of patients after administration of biologic agents is recommended [see Warnings and Precautions (5.1)].

Administer FASENRA into the thigh or abdomen. The upper arm can also be used if a healthcare provider or caregiver administers the injection. Prior to administration, warm FASENRA by leaving carton at room temperature for about 30 minutes. Visually inspect FASENRA for particulate matter and discoloration prior to administration. FASENRA is clear to opalescent, colorless to slightly yellow, and may contain a few translucent or white to off-white particles. Do not use FASENRA if the liquid is cloudy, discolored, or if it contains large particles or foreign particulate matter.

Prefilled Syringe

The prefilled syringe is for administration by a healthcare provider.

Autoinjector (FASENRA PEN™)

FASENRA PEN is intended for administration by patients/caregivers. Patients/caregivers may inject after proper training in subcutaneous injection technique, and after the healthcare provider determines it is appropriate.

In asthma patients aged 6 to 11 years weighing 35 kg or more, FASENRA PEN should only be administered by a caregiver or healthcare provider.

2.4 Instructions for Administration of FASENRA Prefilled Syringe (Healthcare Providers)

Figure 1 FASENRA Prefilled Syringes

Prefilled Syringe Components

To prepare FASENRA prefilled syringe for subcutaneous administration, carefully read and adhere to these instructions for use. FASENRA is available in a 10 mg and a 30 mg prefilled syringe. Check the labels on the FASENRA carton and prefilled syringe to ensure the correct 10 mg or 30 mg product is being used (Figure 1). Refer to Figure 1 to identify the prefilled syringe components for use in the administration steps.

Do not touch the needle guard activation clips to prevent premature activation of the needle safety guard.

1 | Grasp the syringe body, not the plunger, to remove prefilled syringe from the tray. Check the expiration date on the syringe. The syringe may contain small air bubbles; this is normal. Do not expel the air bubbles prior to administration.
2 |  | Do not remove needle cover until ready to inject. Hold the syringe body and remove the needle cover by pulling straight off. Do not hold the plunger or plunger head while removing the needle cover or the plunger may move. If the prefilled syringe is damaged or contaminated (for example, dropped without needle cover in place), discard and use a new prefilled syringe.
3 |  | Gently pinch the skin and insert the needle at the recommended injection site (i.e., upper arm, thigh, or abdomen).
4 |  | Inject all of the medication by pushing in the plunger all the way until the plunger head is completely between the needle guard activation clips. This is necessary to activate the needle guard.
5 |  | After injection, maintain pressure on the plunger head and remove the needle from the skin. Release pressure on the plunger head to allow the needle guard to cover the needle. Do not re-cap the prefilled syringe.
6 | Discard the used syringe into a sharps container.

2.5 Instructions for Administration of FASENRA PEN

Refer to the FASENRA PEN ‘Instructions for Use’ for more detailed instructions on the preparation and administration of FASENRA PEN [see Instructions for Use]. A patient may self-inject or the patient’s caregiver may administer FASENRA PEN subcutaneously after the healthcare provider determines it is appropriate. In patients aged 6 to 11 years weighing 35 kg or more, FASENRA PEN should only be administered by a caregiver or healthcare provider.

3 DOSAGE FORMS AND STRENGTHS

Injection: clear to opalescent, colorless to slightly yellow solution and may contain a few translucent or white to off‑white particles available as:

- 10 mg/0.5 mL solution in a single-dose prefilled syringe.
- 30 mg/mL solution in a single-dose prefilled syringe.
- 30 mg/mL solution in a single-dose autoinjector FASENRA PEN.

4 CONTRAINDICATIONS

FASENRA is contraindicated in patients who have known hypersensitivity to benralizumab or any of its excipients [see Warnings and Precautions (5.1)].

5 WARNINGS AND PRECAUTIONS

5.1 Hypersensitivity Reactions

Hypersensitivity reactions (e.g., anaphylaxis, angioedema, urticaria, rash) have occurred following administration of FASENRA. These reactions generally occur within hours of administration, but in some instances have a delayed onset (i.e., days). In the event of a hypersensitivity reaction, FASENRA should be discontinued [see Contraindications (4)].

5.2 Acute Asthma Symptoms or Deteriorating Disease

FASENRA should not be used to treat acute asthma symptoms or acute exacerbations. Do not use FASENRA to treat acute bronchospasm or status asthmaticus. Patients should seek medical advice if their asthma remains uncontrolled or worsens after initiation of treatment with FASENRA.

5.3 Reduction of Corticosteroid Dosage

Do not discontinue systemic or inhaled corticosteroids (ICS) abruptly upon initiation of therapy with FASENRA. Reductions in corticosteroid dose, if appropriate, should be gradual and performed under the direct supervision of a physician. Reduction in corticosteroid dose may be associated with systemic withdrawal symptoms and/or unmask conditions previously suppressed by systemic corticosteroid therapy.

5.4 Parasitic (Helminth) Infection

Eosinophils may be involved in the immunological response to some helminth infections. Patients with known helminth infections were excluded from participation in clinical trials. It is unknown if FASENRA will influence a patient’s response against helminth infections.

Treat patients with pre-existing helminth infections before initiating therapy with FASENRA. If patients become infected while receiving treatment with FASENRA and do not respond to anti-helminth treatment, discontinue treatment with FASENRA until infection resolves.

6 ADVERSE REACTIONS

The following adverse reactions are described in greater detail in other sections:

- Hypersensitivity Reactions [see Warnings and Precautions (5.1)]

Because clinical trials are conducted under widely varying conditions, adverse reaction rates observed in the clinical trials of a drug cannot be directly compared to rates in the clinical trials of another drug and may not reflect the rates observed in practice.

6.1 Clinical Trials Experience

Adult and Adolescent Patients 12 Years of Age and Older with Asthma

Across three clinical trials (SIROCCO, CALIMA, and ZONDA) for asthma, 1,808 patients received at least 1 dose of FASENRA [see Clinical Studies (14.1)]. The data described below reflect exposure to FASENRA in 1,663 patients, including 1,556 exposed for at least 24 weeks and 1,387 exposed for at least 48 weeks. The safety exposure for FASENRA is derived from two Phase 3 placebo-controlled trials (SIROCCO and CALIMA) from 48 weeks duration [FASENRA every 4 weeks (n=841), FASENRA every 4 weeks for 3 doses, then every 8 weeks (n=822), and placebo (n=847)]. While a dosing regimen of FASENRA every 4 weeks was included in clinical trials, FASENRA administered every 4 weeks for 3 doses, then every 8 weeks thereafter is the recommended dose [see Dosage and Administration (2.1)]. The population studied was 12 to 75 years of age, of which 64% were female and 79% were White.

Adverse reactions that occurred at greater than or equal to 3% incidence are shown in Table 2.

Table 2. Adverse Reactions with FASENRA with Greater than or Equal to 3% Incidence in Patients with Asthma (SIROCCO and CALIMA)
Adverse Reactions | FASENRA; (N=822); % | Placebo; (N=847); %
Headache | 8 | 6
Pyrexia | 3 | 2
Pharyngitis [Pharyngitis was defined by the following terms: ‘Pharyngitis’, ‘Pharyngitis bacterial’, ‘Viral pharyngitis’, ‘Pharyngitis streptococcal’.] | 5 | 3
Hypersensitivity reactions [Hypersensitivity Reactions were defined by the following terms: ‘Urticaria’, ‘Urticaria papular’, and ‘Rash’ [see Warnings and Precautions (5.1)].] | 3 | 3

28-Week Trial

Adverse reactions from ZONDA with 28 weeks of treatment with FASENRA (n=73) or placebo (n=75) in which the incidence was more common in FASENRA than placebo include headache (8.2% compared to 5.3%, respectively) and pyrexia (2.7% compared to 1.3%, respectively) [see Clinical Studies (14.1)]. The frequencies for the remaining adverse reactions with FASENRA were similar to placebo.

Injection Site Reactions in Patients with Asthma

In SIROCCO and CALIMA, the FASENRA 30 mg prefilled syringe was administered at the recommended dosage and injection site reactions (e.g., pain, erythema, pruritus, papule) occurred at a rate of 2.2% in patients treated with FASENRA compared with 1.9% in patients treated with placebo.

Pediatric Patients 6 to 11 Years of Age with Asthma

The safety data for FASENRA is based on a 48-week, open-label, parallel group, pharmacokinetic and pharmacodynamic trial (TATE) of 28 pediatric patients aged 6 to 11 years with severe asthma, and with an eosinophilic phenotype [see Use in Specific Populations (8.4) and Clinical Pharmacology (12.2,12.3)]. Patients received subcutaneous dose of 10 mg (for those weighing less than 35 kg) or 30 mg (for those weighing 35 kg or more) of FASENRA administered every 4 weeks for the first 3 doses, then every 8 weeks thereafter [see Dosage and Administration (2.1)]. No new safety signals were observed in these patients.

Adult Patients with EGPA

The safety of FASENRA is based on 70 adult patients who received at least 1 dose of FASENRA 30 mg administered subcutaneously every 4 weeks in an active-controlled study of 52 weeks duration (MANDARA) [see Clinical Studies (14.2)]. The incidence of adverse reactions were consistent to those reported in asthma, with the exception of headache, which occurred in 17% of FASENRA-treated patients with EGPA. No new adverse reactions were identified.

6.2 Postmarketing Experience

In addition to adverse reactions reported from clinical trials, the following adverse reactions have been identified during post-approval use of FASENRA. Because these reactions are reported voluntarily from a population of uncertain size, it is not always possible to reliably estimate their frequency or establish a causal relationship to drug exposure. These events have been chosen for inclusion due to either their seriousness, frequency of reporting, or causal connection to FASENRA or a combination of these factors.

Immune System Disorders: Hypersensitivity reactions, including anaphylaxis.

7 DRUG INTERACTIONS

No formal drug interaction studies have been conducted.

8 USE IN SPECIFIC POPULATIONS

8.1 Pregnancy

Risk Summary

The data on pregnancy exposure from the clinical trials are insufficient to inform on drug-associated risk. Monoclonal antibodies such as benralizumab are transported across the placenta during the third trimester of pregnancy; therefore, potential effects on a fetus are likely to be greater during the third trimester of pregnancy. In a prenatal and postnatal development study conducted in cynomolgus monkeys, there was no evidence of fetal harm with IV administration of benralizumab throughout pregnancy at doses that produced exposures up to approximately 310 times the exposure at the maximum recommended human dose (MRHD) of 30 mg SC [see Data].

In the U.S. general population, the estimated background risk of major birth defects and miscarriage in clinically recognized pregnancies is 2% to 4% and 15% to 20%, respectively.

Clinical Considerations

Disease-Associated Maternal and/or Embryo/Fetal Risk

In women with poorly or moderately controlled asthma, evidence demonstrates that there is an increased risk of preeclampsia in the mother and prematurity, low birth weight, and small for gestational age in the neonate. The level of asthma control should be closely monitored in pregnant women and treatment adjusted as necessary to maintain optimal control.

Data

Animal Data

In a prenatal and postnatal development study, pregnant cynomolgus monkeys received benralizumab from beginning on GD20 to GD22 (dependent on pregnancy determination), on GD35, once every 14 days thereafter throughout the gestation period and 1-month postpartum (maximum 14 doses) at doses that produced exposures up to approximately 310 times that achieved with the MRHD (on an AUC basis with maternal IV doses up to 30 mg/kg once every 2 weeks). Benralizumab did not elicit adverse effects on fetal or neonatal growth (including immune function) up to 6.5 months after birth. There was no evidence of treatment-related external, visceral, or skeletal malformations. Benralizumab was not teratogenic in cynomolgus monkeys. Benralizumab crossed the placenta in cynomolgus monkeys. Benralizumab concentrations were approximately equal in mothers and infants on postpartum day 7, but were lower in infants at later time points. Eosinophil counts were suppressed in infant monkeys with gradual recovery by 6 months postpartum; however, recovery of eosinophil counts was not observed for one infant monkey during this period.

8.2 Lactation

Risk Summary

There is no information regarding the presence of benralizumab in human or animal milk, and the effects of benralizumab on the breast fed infant and on milk production are not known. However, benralizumab is a humanized monoclonal antibody (IgG1/κ-class), and immunoglobulin G (IgG) is present in human milk in small amounts. If benralizumab is transferred into human milk, the effects of local exposure in the gastrointestinal tract and potential limited systemic exposure in the infant to benralizumab are unknown. The developmental and health benefits of breastfeeding should be considered along with the mother's clinical need for benralizumab and any potential adverse effects on the breast-fed child from benralizumab or from the underlying maternal condition.

8.4 Pediatric Use

Asthma

The safety and effectiveness of FASENRA for add-on maintenance treatment of patients with severe asthma and with an eosinophilic phenotype have been established in pediatric patients 6 years and older. Use of FASENRA for this indication is supported by evidence from the following:

Adolescent Patients 12 to 17 Years of Age

Use of FASENRA in adolescents with severe asthma and with an eosinophilic phenotype is supported by evidence from SIROCCO (n=53) and CALIMA (n=55) that enrolled 108 adolescents aged 12 to 17 years (mean age 14 years, 42% female, White 82%, Asian 2%, Black or African American 4%) with asthma. Of these patients, 46 received placebo, 40 received 30 mg of FASENRA every 4 weeks for 3 doses, followed by every 8 weeks thereafter, and 22 received 30 mg of FASENRA every 4 weeks. Patients were required to weigh 40 kg or more and to have a history of 2 or more asthma exacerbations requiring oral or systemic corticosteroid treatment in the past 12 months and reduced lung function at baseline (pre-bronchodilator FEV1<90%) despite regular treatment with medium or high dose ICS and LABA with or without OCS or other controller therapy [see Clinical Studies (14)]. The pharmacokinetics of benralizumab in adolescents 12 to 17 years of age were consistent with adults based on population pharmacokinetic analysis and the reduction in blood eosinophil counts was similar to that observed in adults following the same FASENRA treatment. The adverse reaction profile in adolescents was generally similar to the overall population in the clinical trials [see Adverse Reactions (6.1)].

Pediatric Patients 6 to 11 Years of Age

Use of FASENRA in pediatric patients aged 6 to 11 years with severe asthma, and with an eosinophilic phenotype is supported by evidence from adequate and well-controlled trials in adults and adolescents with additional pharmacokinetic, pharmacodynamic, and safety data in pediatric patients aged 6 to 11 years. The effectiveness of FASENRA in pediatric patients 6 to 11 years of age is extrapolated from efficacy in three clinical trials (SIROCCO, CALIMA, and ZONDA) [see Clinical Studies (14)] with support from pharmacokinetic analysis and pharmacodynamic response in pediatric patients aged 6 to 11 years compared to adults and adolescents. TATE is a 48-week, open-label, pharmacokinetic and pharmacodynamic trial that was conducted in 28 patients aged 6 to 11 years (mean age 9 years; 6-8 years, n=11; 9-11 years n=17; 32% female, White 29%, Asian 32%, Black or African American 29%) with severe asthma, and with an eosinophilic phenotype.

Based upon the pharmacokinetic data from TATE, a subcutaneous dose of 10 mg (patients <35 kg) and subcutaneous dose of 30 mg (patients ≥35 kg) of benralizumab administered every 4 weeks for the first 3 doses, then every 8 weeks thereafter in patients aged 6 to 11 years was determined to have similar or higher exposure, respectively, to adults and adolescents administered a subcutaneous dose of 30 mg with the same dosing regimen [see Clinical Pharmacology (12.3)]. The pharmacodynamic response observed in TATE for pediatric patients aged 6 to 11 years was similar to that observed in adults and adolescents [see Clinical Pharmacology (12.2)]. No new safety signals were observed from TATE and safety for the higher drug exposure is supported by safety data from SIROCCO and CALIMA in adults and adolescents, and ZONDA in adults, who received 30 mg of FASENRA every 4 weeks for 1 year.

The safety and effectiveness in patients younger than 6 years of age have not been established.

EGPA

The safety and effectiveness of FASENRA in patients with EGPA younger than 18 years of age have not been established.

8.5 Geriatric Use

Asthma

Of the total number of patients in asthma clinical trials of benralizumab, 13% (n=320) were 65 and over, while 0.4% (n=9) were 75 and over. No overall differences in safety or effectiveness were observed between these patients and younger patients, and other reported clinical experience has not identified differences in responses between the elderly and younger patients, but greater sensitivity of some older individuals cannot be ruled out.

EGPA

Of the 70 patients with EGPA exposed to FASENRA, a total of 13 (19%) were 65 years or older. Clinical studies of FASENRA for EGPA did not include sufficient numbers of subjects aged 65 and over to determine whether they respond differently from younger subjects.

10 OVERDOSAGE

There is no specific treatment for an overdosage with benralizumab. If overdose occurs, the patient should be treated supportively with appropriate monitoring as necessary.

11 DESCRIPTION

Benralizumab is a humanized monoclonal antibody (IgG1/κ-class) selective for interleukin-5 receptor alpha subunit (IL-5Rα). Benralizumab is produced in Chinese hamster ovary cells by recombinant DNA technology. Benralizumab has a molecular weight of approximately 150 kDa.

FASENRA (benralizumab) injection is a sterile, preservative-free, clear to opalescent, colorless to slightly yellow solution for subcutaneous injection. Since benralizumab is a protein, a few translucent or white to off-white particles may be present in the solution.

Each 10 mg single-dose prefilled syringe delivers 0.5 mL containing 10 mg benralizumab, L-histidine (0.7 mg); L-histidine hydrochloride monohydrate (1.2 mg); polysorbate 20 (0.03 mg); α,α‑trehalose dihydrate (47 mg); and Water for Injection, USP, at pH of 5.5 – 6.5. The single-dose prefilled syringe contains a 1 mL glass syringe with a staked 29 gauge ½ inch stainless steel needle.

Each 30 mg single-dose prefilled syringe or single-dose autoinjector delivers 1 mL containing 30 mg benralizumab, L-histidine (1.4 mg); L-histidine hydrochloride monohydrate (2.3 mg); polysorbate 20 (0.06 mg); α,α‑trehalose dihydrate (95 mg); and Water for Injection, USP, at pH of 5.5 – 6.5. The single-dose prefilled syringe or single-dose autoinjector contains a 1 mL glass syringe with a staked 29 gauge ½ inch stainless steel needle.

12 CLINICAL PHARMACOLOGY

12.1 Mechanism of Action

Benralizumab is a humanized afucosylated, monoclonal antibody (IgG1, kappa) that directly binds to the alpha subunit of the human interleukin-5 receptor (IL-5Rα) with a dissociation constant of 11 pM. The IL-5 receptor is expressed on the surface of eosinophils and basophils. In an in vitro setting, the absence of fucose in the Fc domain of benralizumab facilitates binding (45.5 nM) to FcɣRIII receptors on immune effector cells, such as natural killer (NK) cells, leading to apoptosis of eosinophils and basophils through antibody-dependent cell-mediated cytotoxicity (ADCC).

Inflammation is an important component in the pathogenesis of asthma and EGPA. Multiple cell types (e.g., mast cells, eosinophils, neutrophils, macrophages, lymphocytes) and mediators (e.g., histamine, eicosanoids, leukotrienes, cytokines) are involved in inflammation. Benralizumab, by binding to the IL-5Rα chain, reduces eosinophils through ADCC; however, the mechanism of benralizumab action in asthma and EGPA has not been definitively established.

12.2 Pharmacodynamics

In the 52-week Phase 2 dose-ranging trial, asthma patients received 1 of 3 doses of benralizumab [2 mg (n=81), 20 mg (n=81), or 100 mg (n=222)] or placebo (n=222). All doses were administered every 4 weeks for the first 3 doses, followed by every 8 weeks thereafter. Median blood eosinophil levels at baseline were 310, 280, 190 and 190 cells/μL in the 2, 20, and 100 mg benralizumab and placebo groups, respectively. Dose-dependent reductions in blood eosinophils were observed. At the time of the last dose (Week 40), median blood eosinophil counts were 100, 50, 40, 170 cells/μL in the 2, 20, and 100 mg benralizumab and placebo groups, respectively.

A reduction in blood eosinophil counts was observed 24 hours post dosing in an asthma Phase 2 trial.

In SIROCCO and CALIMA, following SC administration of benralizumab at the recommended dose blood eosinophils were reduced to a median absolute blood eosinophil count of 0 cells/μL [see Clinical Studies (14)]. This magnitude of reduction was observed at the first time point, 4 weeks of treatment, and was maintained throughout the treatment period.

Treatment with benralizumab was also associated with reductions in blood basophils, which was consistently observed across all asthma clinical studies. In the Phase 2 dose-ranging asthma trial, blood basophil counts were measured by flow cytometry. Median blood basophil counts were 45, 52, 46, and 40 cells/µL in the 2 mg, 20 mg and 100 mg benralizumab and placebo groups, respectively. At 52 weeks (12 weeks after the last dose), median blood basophil counts were 42, 18, 17, and 46 cells/µL in the 2 mg, 20 mg and 100 mg benralizumab and placebo groups, respectively.

In TATE, a 48-week trial with patients aged 6 to 11 years who had severe asthma, and with an eosinophilic phenotype [see Use in Specific Populations (8.4)], the magnitude of blood eosinophil reduction was similar to that observed in adults and adolescents. Median blood eosinophil levels at baseline were 400 and 340 cells/µL in patients weighing <35 kg and ≥35 kg, respectively. Across all post-dose time points, median eosinophil counts reduced to 10 to 20 cells/µL in patients weighing <35 kg, and to 20 to 30 cells/µL in patients weighing ≥35 kg. Blood eosinophil reduction was observed at the first time point, 4 weeks of treatment, and was maintained throughout the treatment period.

In patients with EGPA, reduction of blood eosinophils was consistent with the effect observed in asthma trials. Median absolute blood eosinophil levels in the benralizumab group at baseline were 240 cells/μL. Following SC administration of benralizumab at the recommended dosage in patients with EGPA, blood eosinophils were reduced to a median absolute blood eosinophil count of 20 to 30 cells/μL. Blood eosinophil reduction was seen at the first observed time point, 1 week of treatment, and was maintained throughout the 52‑week treatment period.

12.3 Pharmacokinetics

The pharmacokinetic properties of benralizumab below are based on the population pharmacokinetic analyses from the asthma trials. Findings in EGPA were generally consistent with those in asthma although a lower clearance is predicted for patients with EGPA relative to patients with asthma [see Elimination].

The pharmacokinetics of benralizumab was approximately dose-proportional in adult and adolescent patients with asthma following subcutaneous administration over a dose range of 20 to 200 mg.

Absorption

Following subcutaneous administration to patients with asthma, the absorption half-life was approximately 3.5 days. Based on population pharmacokinetic analysis, the estimated absolute bioavailability was approximately 59% and there was no clinically relevant difference in relative bioavailability in the administration to the abdomen, thigh, or arm.

Distribution

Based on population pharmacokinetic analysis, central and peripheral volume of distribution of benralizumab was 3.1 L and 2.5 L, respectively, for a 70 kg individual.

Elimination

From population pharmacokinetic analysis, benralizumab exhibited linear pharmacokinetics and no evidence of target receptor-mediated clearance pathway. The estimated typical systemic clearance (CL) for benralizumab was 0.29 L/d for an asthma patient weighing 70 kg. The estimated typical CL was 0.22 L/d for patients with EGPA. Following subcutaneous administration in patients with asthma, the elimination half-life was approximately 15.5 days.

Metabolism

Benralizumab is a humanized IgG1 monoclonal antibody that is degraded by proteolytic enzymes widely distributed in the body and not restricted to hepatic tissue.

Specific populations:

Age

Based on population pharmacokinetic analysis, age did not affect benralizumab clearance.

Gender, Race

A population pharmacokinetics analysis indicated that there was no significant effect of gender and race on benralizumab clearance.

Patients with Renal impairment

No formal clinical studies have been conducted to investigate the effect of renal impairment on benralizumab. Based on population pharmacokinetic analysis, benralizumab clearance was comparable in subjects with creatinine clearance values between 30 and 80 mL/min and patients with normal renal function. There are limited data available in subjects with creatinine clearance values less than 30 mL/min; however, benralizumab is not cleared renally.

Patients with Hepatic impairment

No formal clinical studies have been conducted to investigate the effect of hepatic impairment on benralizumab. IgG monoclonal antibodies are not primarily cleared via hepatic pathway; change in hepatic function is not expected to influence benralizumab clearance. Based on population pharmacokinetic analysis, baseline hepatic function biomarkers (ALT, AST, and bilirubin) had no clinically relevant effect on benralizumab clearance.

Pediatric Patients

Benralizumab pharmacokinetics following subcutaneous administration of 10 mg or 30 mg in patients aged 6 to 11 years with severe asthma and with an eosinophilic phenotype asthma was investigated in the initial 16-week treatment phase of TATE, a 48-week open-label trial. Among patients aged 6 to 11 years weighing <35 kg who received 10 mg, the median trough concentration at Week 16 was similar to that of adults and adolescents who received 30 mg. Among patients aged 6 to 11 years weighing ≥35 kg who received 30 mg, the median trough concentration at Week 16 was 62% higher relative to adults and adolescents receiving the same dose, due to lower body weight in pediatric patients.

Drug Interaction Studies

No formal drug-drug interaction studies have been conducted.

Cytochrome P450 enzymes, efflux pumps and protein-binding mechanisms are not involved in the clearance of benralizumab. There is no evidence of IL-5Rα expression on hepatocytes and eosinophil depletion does not produce chronic systemic alterations of proinflammatory cytokines.

An effect of benralizumab on the pharmacokinetics of co-administered medications is not expected. Based on the population analysis, commonly co-administered medications had no effect on benralizumab clearance in patients with asthma.

12.6 Immunogenicity

The observed incidence of anti-drug antibodies (ADA) is highly dependent on the sensitivity and specificity of the assay. Differences in assay methods preclude meaningful comparisons of the incidence of ADA in the studies described below with the incidence of ADA in other studies, including those of benralizumab or of other benralizumab products.

In adult and adolescent patients with asthma, the incidence of ADA to benralizumab in patients treated with FASENRA at the recommended dosing regimen during the 48 to 56‑week treatment period was 13%. A total of 12% of patients treated with FASENRA developed neutralizing antibodies.

In pediatric patients 6 to 11 years with severe asthma and with an eosinophilic phenotype, the incidence of ADA to benralizumab during an open-label 48-week treatment period was comparable to adult and adolescent patients.

In patients with EGPA, the incidence of ADA to benralizumab during the active-controlled 52-week treatment period was 9% (6 out of 67 patients). Neutralizing antibody activity was detected in one of the ADA positive patients.

Anti-Drug Antibody Effects on Pharmacokinetics and Pharmacodynamics

Anti-benralizumab antibodies were associated with increased clearance of benralizumab and increased blood eosinophil levels in asthma patients with high ADA titers compared to antibody negative patients. Reduced benralizumab trough concentrations were observed in one EGPA patient with high ADA titers.

In the asthma trials with adult and adolescent patients and in the EGPA trial, no evidence of an association of ADA with efficacy or safety was observed.

13 NONCLINICAL TOXICOLOGY

13.1 Carcinogenesis, Mutagenesis, Impairment of Fertility

Long-term animal studies have not been performed to evaluate the carcinogenic potential of benralizumab. Published literature using animal models suggests that IL-5 and eosinophils are part of an early inflammatory reaction at the site of tumorigenesis and can promote tumor rejection. However, other reports indicate that eosinophil infiltration into tumors can promote tumor growth. Therefore, the malignancy risk in humans from an antibody that binds to IL-5Rα such as benralizumab is unknown.

Male and female fertility were unaffected based upon no adverse histopathological findings in the reproductive organs from cynomolgus monkeys treated with benralizumab for 9 months at IV doses up to 25 mg/kg or at SC doses of up to 30 mg/kg once every 2 weeks (approximately 400 and 270 times the MRHD on an AUC basis).

14 CLINICAL STUDIES

14.1 Clinical Studies in Patients with Asthma

The efficacy of FASENRA for the add-on maintenance treatment of severe asthma, and with an eosinophilic phenotype was evaluated in two randomized, double-blind, parallel-group, placebo-controlled, exacerbation trials, SIROCCO (NCT01928771) and CALIMA (NCT01914757), for 48 and 56 weeks in duration, respectively. Furthermore, the effects of FASENRA in the reduction of oral corticosteroid use and effect on lung function were evaluated in clinical trials, ZONDA (NCT02075255) and a 12-week lung function trial (NCT02322775), respectively.

SIROCCO and CALIMA were randomized, double-blind, parallel-group, placebo-controlled, exacerbation trials in patients 12 years of age and older and 48 and 56 weeks in duration, respectively. The trials randomized a total of 2,510 patients. Patients were required to have a history of 2 or more asthma exacerbations requiring oral or systemic corticosteroid treatment in the past 12 months, ACQ‑6 score of 1.5 or more at screening, and reduced lung function at baseline [pre-bronchodilator FEV1 below 80% in adults, and below 90% in adolescents] despite regular treatment with high dose ICS (SIROCCO) or with medium or high dose ICS (CALIMA) plus a long-acting beta agonist (LABA) with or without oral corticosteroids (OCS) and additional asthma controller medications. Patients were stratified by geography, age, and blood eosinophils count (≥300 cells/μL or <300 cells/μL). FASENRA administered once every 4 weeks for the first 3 doses, and then every 4 or 8 weeks thereafter as add-on to background treatment was evaluated compared to placebo.

All subjects continued their background asthma therapy throughout the duration of the trials.

ZONDA was a randomized, double-blind, parallel-group, OCS reduction trial in 220 adult patients with asthma. Patients were required treatment with daily OCS (7.5 to 40 mg per day) in addition to regular use of high-dose ICS and LABA with or without additional controller(s). The trial included an 8‑week run-in period during which the OCS was titrated to the minimum effective dose without losing asthma control. For the purposes of the OCS dose titration, asthma control was assessed by the investigator based on a patient’s FEV1, peak expiratory flow, nighttime awakenings, short-acting bronchodilator rescue medication use or any other symptoms that would require an increase in OCS dose. Baseline median OCS dose was similar across all treatment groups. Patients were required to have blood eosinophil counts greater than or equal to 150 cells/μL and a history of at least one exacerbation in the past 12 months. The baseline median OCS dose was 10 mg (range: 8 to 40 mg) for all 3 treatment groups (placebo, FASENRA every 4 weeks, and FASENRA every 4 weeks for the first 3 doses, and then once every 8 weeks).

While 2 dosing regimens were studied in SIROCCO, CALIMA, and ZONDA, the recommended dosing regimen is 30 mg FASENRA administered every 4 weeks for the first 3 doses, then every 8 weeks thereafter [see Dosage and Administration (2.1)].

Table 3. Demographics and Baseline Characteristics of Asthma Trials
 | Total Population
 | SIROCCO; (N=1204) | CALIMA; (N=1306) | ZONDA; (N=220)
Mean age (yr) | 49 | 49 | 51
Female (%) | 66 | 62 | 61
White (%) | 73 | 84 | 93
Duration of asthma, median (yr) | 15 | 16 | 12
Never smoked (%) | 80 | 78 | 79
Mean baseline FEV1 pre-bronchodilator (L) | 1.67 | 1.76 | 1.85
Mean baseline % predicted FEV1 | 57 | 58 | 60
Mean post-SABA FEV1/FVC (%) | 66 | 65 | 62
Mean baseline eosinophil count (cells/μL) | 472 | 472 | 575
Mean number of exacerbations in previous year | 3 | 3 | 3

Exacerbations

The primary endpoint for SIROCCO and CALIMA was the rate of asthma exacerbations in patients with baseline blood eosinophil counts of greater than or equal to 300 cells/μL who were taking high‑dose ICS and LABA. Asthma exacerbation was defined as a worsening of asthma requiring use of oral/systemic corticosteroids for at least 3 days, and/or emergency department visits requiring use of oral/systemic corticosteroids and/or hospitalization. For patients on maintenance oral corticosteroids, an asthma exacerbation requiring oral corticosteroids was defined as a temporary increase in stable oral/systemic corticosteroids for at least 3 days or a single depo-injectable dose of corticosteroids. In SIROCCO, 35% of patients receiving FASENRA experienced an asthma exacerbation compared to 51% on placebo. In CALIMA, 40% of patients receiving FASENRA experienced an asthma exacerbation compared to 51% on placebo (Table 4).

Table 4. Rate of Exacerbations, SIROCCO and CALIMA (ITT Population) [Baseline blood eosinophil counts of greater than or equal to 300 cells/μL and taking high-dose ICS]
Trial | Treatment | Exacerbations per year
 |  | Rate | Difference | Rate Ratio (95% CI)
All exacerbations
SIROCCO | FASENRA [FASENRA 30 mg administered every 4 weeks for the first 3 doses, and every 8 weeks thereafter] (n=267) | 0.74 | -0.78 | 0.49 (0.37, 0.64)
SIROCCO | Placebo (n=267) | 1.52 | -- | --
CALIMA | FASENRA (n=239) | 0.73 | -0.29 | 0.72 (0.54, 0.95)
CALIMA | Placebo (n=248) | 1.01 | -- | --
Exacerbations requiring hospitalization/emergency room visit
SIROCCO | FASENRA (n=267) | 0.09 | -0.16 | 0.37 (0.20, 0.67)
SIROCCO | Placebo (n=267) | 0.25 | -- | --
CALIMA | FASENRA (n=239) | 0.12 | 0.02 | 1.23 (0.64, 2.35)
CALIMA | Placebo (n=248) | 0.10 | -- | --
Exacerbations requiring hospitalization
SIROCCO | FASENRA (n=267) | 0.07 | -0.07 | 0.48 (0.22, 1.03)
SIROCCO | Placebo (n=267) | 0.14 | -- | --
CALIMA | FASENRA (n=239) | 0.07 | 0.02 | 1.48 (0.65, 3.37)
CALIMA | Placebo (n=248) | 0.05 | -- | --

The time to first exacerbation was longer for the patients receiving FASENRA compared with placebo in SIROCCO (Figure 2). Similar findings were seen in CALIMA.

Figure 2. Kaplan-Meier Cumulative Incidence Curves for Time to First Exacerbation, SIROCCO

Subgroup analyses from SIROCCO and CALIMA identified patients with a higher prior exacerbation history and baseline blood eosinophil count as potential predictors of improved treatment response. Reductions in exacerbation rates were observed irrespective of baseline peripheral eosinophil counts; however, patients with a baseline blood eosinophil count ≥300 cells/μL showed a numerically greater response than those with counts <300 cells/μL. In both trials patients with a history of 3 or more exacerbations within the 12 months prior to FASENRA randomization showed a numerically greater exacerbation response than those with fewer prior exacerbations.

Oral Corticosteroid Reduction

ZONDA evaluated the effect of FASENRA on reducing the use of maintenance oral corticosteroids in adult patients with asthma. The primary endpoint was percent reduction from baseline of the final OCS dose during Weeks 24 to 28, while maintaining asthma control (see definition of asthma control in trial description). Compared to placebo, patients receiving FASENRA achieved greater reductions in daily maintenance oral corticosteroid dose, while maintaining asthma control. The median percent reduction in daily OCS dose from baseline was 75% in patients receiving FASENRA (95% CI: 60, 88) compared to 25% in patients receiving placebo (95% CI: 0, 33). Reductions of 50% or higher in the OCS dose were observed in 48 (66%) patients receiving FASENRA compared to those receiving placebo 28 (37%). The proportion of patients with a mean final dose less than or equal to 5 mg at Weeks 24 to 28 was 59% for FASENRA and 33% for placebo (odds ratio 2.74, 95% CI: 1.41, 5.31). Only patients with an optimized baseline OCS dose of 12.5 mg or less were eligible to achieve a 100% reduction in OCS dose during the study. Of those patients, 52% (22 of 42) receiving FASENRA and 19% (8 of 42) on placebo achieved a 100% reduction in OCS dose. Exacerbations resulting in hospitalization and/or ER visit were also assessed as a secondary endpoint. In this 28-week trial, patients receiving FASENRA had 1 event while those on placebo had 14 events (annualized rate 0.02 and 0.32, respectively; rate ratio of 0.07, 95% CI: 0.01, 0.63).

Lung Function

Change from baseline in mean FEV1 was assessed in SIROCCO, CALIMA, and ZONDA as a secondary endpoint. Compared with placebo, FASENRA provided consistent improvements over time in the mean change from baseline in FEV1 (Figure 3 and Table 5).

Figure 3. Mean Change from Baseline in Pre-Bronchodilator FEV1 (L), CALIMA

Table 5. Change from Baseline in Mean Pre-Bronchodilator FEV1 (L) at End of Trial [Week 48 in SIROCCO, Week 56 in CALIMA, Week 28 in ZONDA.]
Trial | Difference from Placebo in Mean Change from Pre-Bronchodilator Baseline FEV1 (L) (95% CI)
SIROCCO | 0.159 (0.068, 0.249)
CALIMA | 0.116 (0.028, 0.204)
ZONDA | 0.112 (-0.033, 0.258)

Subgroup analyses also showed greater improvements in FEV1 in patients with higher baseline blood eosinophil counts and more frequent prior exacerbation history.

The clinical program for FASENRA also included a 12-week, randomized, double-blind, placebo-controlled lung function trial conducted in 211 adult patients with mild to moderate asthma. Patients were treated with placebo or benralizumab 30 mg SC every 4 weeks for 3 doses. Lung function, as measured by the change from baseline in FEV1 at Week 12 was improved in the benralizumab treatment group compared to placebo.

Patient Reported Outcomes

The Asthma Control Questionnaire-6 (ACQ-6) and Standardized Asthma Quality of Life Questionnaire for 12 Years and Older (AQLQ(S)+12) were assessed in SIROCCO, CALIMA, and ZONDA. The responder rate for both measures was defined as improvement in score of 0.5 or more as threshold at the end of SIROCCO, CALIMA, and ZONDA (48, 56, and 28 weeks, respectively). In SIROCCO, the ACQ-6 responder rate for FASENRA was 60% vs 50% placebo (odds ratio 1.55; 95% CI: 1.09, 2.19). In CALIMA, the ACQ-6 responder rate for FASENRA was 63% vs 59% placebo (odds ratio 1.16; 95% CI: 0.80, 1.68). In SIROCCO, the responder rate for AQLQ(S)+12 for FASENRA was 57% vs 49% placebo (odds ratio 1.42; 95% CI: 0.99, 2.02), and in CALIMA, 60% FASENRA vs 59% placebo (odds ratio of 1.03; 95% CI: 0.70,1.51). Similar results were seen in ZONDA.

14.2 Clinical Studies in Patients with Eosinophilic Granulomatosis with Polyangiitis

The efficacy of FASENRA for eosinophilic granulomatosis with polyangiitis (EGPA) was evaluated in a randomized, double-blind, active-controlled, noninferiority clinical trial (MANDARA [NCT04157348]) of 52‑weeks duration. The trial enrolled a total of 140 adults aged 18 years and older with EGPA. Patients were required to have asthma, eosinophilia (1,000 cells/uL or >10% of leukocytes) and a history of relapsing or refractory disease treated with background prednisolone/prednisone with or without immunosuppressive therapy. Patients were randomized to receive FASENRA 30 mg administered subcutaneously every 4 weeks or mepolizumab 300 mg administered subcutaneously every 4 weeks in addition to continued background therapy. Starting at Week 4, the oral corticosteroid (OCS) dose was tapered at the discretion of the investigator. The MANDARA trial was a non-inferiority trial and was not designed to assess whether FASENRA was superior to mepolizumab. The pre-specified noninferiority (NI) margin was a treatment difference of ‑25%. The secondary endpoints (accrued duration of remission, relapse, OCS reduction and the asthma control questionnaire-6) were not included in the pre-specified multiple testing procedure for statistical significance.

The demographics and baseline characteristics of patients in MANDARA are provided in Table 6.

Table 6. Demographics and Baseline Characteristics of Patients with EGPA in the MANDARA Trial
 | MANDARA (N=140)
Mean age (years) | 52
Female (%) | 60
White (%) | 79
Asian (%) | 12
Other (%) | 4
Hispanic or Latino (%) | 3
Time since diagnosis of EGPA, years, mean (SD) | 5.2 (5.6)
History of ≥1 confirmed relapse in past 2 years (%) | 79
Refractory disease (%) | 60
Baseline oral corticosteroid [Prednisone or prednisolone equivalent.] daily dose, mg, median (range) | 10 (5 - 40)
Baseline BVAS, median (range) | 0 (0 – 18)
BVAS=0 (%) | 52
Receiving immunosuppressive therapy [Azathioprine, methotrexate, mycophenolic acid.] (%) | 36
ANCA positive [Anti-neutrophil cytoplasmic antibody (ANCA) positive historically or at screening.] (%) | 29
Biopsy Evidence of Eosinophilic Vasculitis/Inflammation (%) | 38
SD=standard deviation; BVAS=Birmingham vasculitis activity score.

Remission

The primary endpoint in MANDARA was the proportion of patients in remission, defined as Birmingham Vasculitis Activity Score (BVAS)=0 (no active vasculitis) plus prednisolone/prednisone dose ≤4 mg/day, at both Week 36 and Week 48. The BVAS is a clinician-completed tool, that is divided into 9 organ-based systems, to assess clinically active vasculitis that would likely require treatment, after exclusion of other causes. As shown in Table 7, FASENRA demonstrated noninferiority to mepolizumab for the primary endpoint of remission and the components of remission.

Table 7. Remission and Components of Remission in Patients with EGPA in MANDARA Trial
 | Remission; (OCS≤4 mg/day + BVAS=0) |  | OCS≤4 mg/day |  | BVAS=0
 | FASENRA [FASENRA 30 mg administered subcutaneously every 4 weeks.]; N=70 | Mepo [Mepolizumab (Mepo) 300 mg administered subcutaneously every 4 weeks.]; N=70 | FASENRA; N=70 | Mepo; N=70 | FASENRA; N=70 | Mepo; N=70
Patients in remission at both Weeks 36 and 48
Patients, n (%) [Model adjusted percentages.] | 41 (59) | 40 (57) | 43 (62) | 41 (58) | 58 (83) | 59 (84)
Differences in remission rate (%); (95% CI) | 2.7 | -- | 4.1 | -- | -1.2 | --
Differences in remission rate (%); (95% CI) | (-13, 18) [NI margin -25% with 2.5% 1 sided significance level. Since the lower bound of the 95% CI for the treatment difference was >-25%, effectiveness of FASENRA was demonstrated to be noninferior to the effectiveness of mepolizumab.] | -- | (-11, 19) | -- | (-13, 11) | --
N=number of patients in analysis.

Using an alternative remission definition of BVAS=0 plus prednisolone/ prednisone ≤7.5 mg/day, consistent efficacy between groups for these endpoints was observed.

Accrued Duration of Remission

Total accrued duration of remission was similar in FASENRA compared to mepolizumab (odds ratio 1.4, 95% CI: 0.75, 2.5). Results for accrued duration of remission are shown in Table 8. The proportion of patients achieving remission within the first 24 weeks of treatment and remaining in remission through Week 52 was 42% for FASENRA and 37% for mepolizumab (difference in responder rate 5.5%, 95% CI: -9.3, 20). This result was not statistically significant as there was no pre-specified multiple testing procedure.

Table 8. Accrued Duration of Remission in Patients with EGPA in the MANDARA Trial
 | Remission; (OCS≤4 mg/day +; BVAS=0) |  | OCS≤4 mg/day |  | BVAS=0
 | FASENRA [FASENRA 30 mg administered subcutaneously every 4 weeks.]; N=70 | Mepo [Mepolizumab (Mepo) 300 mg administered subcutaneously every 4 weeks.]; N=70 | FASENRA; N=70 | Mepo; N=70 | FASENRA; N=70 | Mepo; N=70
Accrued duration over 52 weeks [Not included in the pre-specified multiple testing procedure for statistical significance.] , n (%)
0 weeks [Did not achieve remission at any point.]; >0 to <12 weeks; 12 to <24 weeks; 24 to <36 weeks; ≥36 weeks | 9 (13); 12 (17); 8 (11); 21 (30); 20 (29) | 15 (21); 10 (14); 8 (11); 19 (27); 18 (26) | 9 (13); 10 (14); 9 (13); 19 (27); 23 (33) | 12 (17); 12 (17); 8 (11); 18 (26); 20 (29) | 0; 0; 2 (3); 6 (9); 62 (89) | 0; 2 (3); 2 (3); 7 (10); 59 (84)
Odds ratio [An odds ratio >1 favors FASENRA. This result was not statistically significant as there was no pre-specified multiple testing procedure.] (95% CI) | 1.4; (0.75, 2.5) | --; -- | 1.4; (0.74, 2.5) | --; -- | 1.5; (0.54, 4.2) | --; --

Relapse

The hazard ratio for time to first relapse (defined as worsening related to vasculitis, asthma, or sino-nasal symptoms requiring an increase in dose of corticosteroids or immunosuppressive therapy or hospitalization) was 0.98 (95% CI: 0.53, 1.8). Relapse was observed in 30% of patients on FASENRA and 30% of patients on mepolizumab. The annualized relapse rate was 0.50 for patients receiving FASENRA versus 0.49 for patients receiving mepolizumab (rate ratio 1.0, 95% CI: 0.56, 1.9). The types of relapse were consistent for patients receiving FASENRA or mepolizumab.

Oral Corticosteroid Reduction

During Weeks 48 to 52, a 100% reduction in the OCS dose was observed in 41% of patients receiving FASENRA compared to 26% of those receiving mepolizumab (difference 16%, 95% CI: 0.67, 31). During Weeks 48 to 52, reductions of 50% or higher were observed in 86% of patients receiving FASENRA compared to 74% of those receiving mepolizumab (difference 12%, 95% CI: -0.57, 25). These results were not statistically significant as there was no pre‑specified multiple testing procedure.

Asthma Control Questionnaire-6 (ACQ-6)

ACQ-6 is a 6-item questionnaire that is completed by the patient to measure the adequacy of asthma control and change in asthma control. The ACQ-6 responder rate during Weeks 48 to 52 (defined as a decrease in score of 0.5 or more compared with baseline) was 42% for FASENRA and 48% for mepolizumab (difference -6.2%, 95% CI: -19, 6.2).

16 HOW SUPPLIED/STORAGE AND HANDLING

How Supplied

FASENRA (benralizumab) injection is a sterile, preservative-free, clear to opalescent, colorless to slightly yellow solution and may contain a few translucent or white to off-white particles, for subcutaneous injection supplied as a single-dose prefilled syringe or single-dose autoinjector. The prefilled syringe (including stopper and cap) and autoinjector are not made with natural rubber latex.

FASENRA is available as:

Single-Dose Prefilled Syringe

- Carton contains one 10 mg/0.5 mL single-dose prefilled syringe with a gray plunger rod: NDC 0310-1745-01
- Carton contains one 30 mg/mL single-dose prefilled syringe with a blue plunger rod: NDC 0310-1730-30

Single-Dose Autoinjector FASENRA PEN

- Carton contains one 30 mg/mL single-dose autoinjector: NDC 0310-1830-30

Storage and Handling

Store refrigerated at 36°F to 46°F (2°C to 8°C) in the original carton to protect from light.

If needed, the prefilled syringe and autoinjector may be stored at room temperature up to 77°F (25°C) for a maximum of 14 days in the original carton to protect from light. Once removed from the refrigerator and brought to room temperature (up to 77°F [25°C]), the prefilled syringe and autoinjector must be used within 14 days or discarded.

Do not freeze. Do not shake. Do not expose to heat.

17 PATIENT COUNSELING INFORMATION

Advise the patients and/or caregivers to read the FDA-approved patient labeling (Patient Information and Instructions for Use for FASENRA PEN) before the patient starts using FASENRA and each time the prescription is renewed as there may be new information they need to know.

Administration Instructions

Instruct patients and/or caregivers on proper subcutaneous injection technique using the FASENRA PEN, including aseptic technique, and the preparation and administration of FASENRA PEN prior to use. Advise patients to follow sharps disposal recommendations [see Instructions for Use].

Hypersensitivity Reactions

Inform patients that hypersensitivity reactions (e.g., anaphylaxis, angioedema, urticaria, rash) have occurred after administration of FASENRA. These reactions generally occurred within hours of FASENRA administration, but in some instances had a delayed onset (i.e., days). Instruct patients to contact their healthcare provider if they experience symptoms of an allergic reaction [see Warnings and Precautions (5.1)].

Not for Acute Symptoms or Deteriorating Disease

Inform patients that FASENRA does not treat acute asthma symptoms or acute exacerbations. Inform patients to seek medical advice if their asthma remains uncontrolled or worsens after initiation of treatment with FASENRA [see Warnings and Precautions (5.2)].

Reduction of Corticosteroid Dosage

Inform patients to not discontinue systemic or inhaled corticosteroids except under the direct supervision of a physician. Inform patients that reduction in corticosteroid dose may be associated with systemic withdrawal symptoms and/or unmask conditions previously suppressed by systemic corticosteroid therapy [see Warnings and Precautions (5.3)].

Manufactured by

AstraZeneca AB

Södertälje, Sweden SE-15185

US License No. 2059

Distributed by

AstraZeneca Pharmaceuticals LP,

Wilmington, DE 19850

FASENRA is a trademark of the AstraZeneca group of companies.

©AstraZeneca 2024

Patient Information

FASENRA® (fas-en-rah)

(benralizumab)

injection, for subcutaneous use

What is FASENRA?

FASENRA is a prescription medicine used:

  - with other asthma medicines for the maintenance treatment of asthma in people 6 years and older whose asthma is not controlled with their current asthma medicines. FASENRA helps prevent severe asthma attacks (exacerbations) and may improve your breathing.
  - to treat people 18 years and older with eosinophilic granulomatosis with polyangiitis (EGPA).
- FASENRA reduces blood eosinophils. Eosinophils are a type of white blood cell that may contribute to your condition.
- FASENRA is not used to treat sudden breathing problems.
- Tell your healthcare provider if your asthma does not get better or if it gets worse after you start treatment with FASENRA.

It is not known if FASENRA is safe and effective in children with asthma under 6 years of age.

It is not known if FASENRA is safe and effective in children with EGPA under 18 years of age.

Do not use FASENRA if you are allergic to benralizumab or any of the ingredients in FASENRA. See the end of this leaflet for a complete list of ingredients in FASENRA.

Before using FASENRA, tell your healthcare provider about all of your medical conditions, including if you:

- are taking oral or inhaled corticosteroid medicines. Do not stop taking your corticosteroid medicines unless instructed by your healthcare provider. This may cause other symptoms that were controlled by the corticosteroid medicine to come back.
- have a parasitic (helminth) infection.
- are pregnant or plan to become pregnant. It is not known if FASENRA will harm your unborn baby. Tell your healthcare provider if you become pregnant during your treatment with FASENRA.
- are breastfeeding or plan to breastfeed. It is not known if FASENRA passes into your breast milk. You and your healthcare provider should decide if you will use FASENRA and breastfeed. Talk to your healthcare provider about the best way to feed your baby if you use FASENRA.

Tell your healthcare provider about all the medicines you take, including prescription and over-the-counter medicines, vitamins, and herbal supplements.

Do not stop taking your other medicines for your condition unless your healthcare provider tells you to.

How will I use FASENRA?

- FASENRA is injected under your skin (subcutaneously):
  - one time every 4 weeks for the first 3 doses and then every 8 weeks, for asthma.
  - one time every 4 weeks for EGPA.
- FASENRA comes in a single dose prefilled syringe and in a single dose autoinjector.
- A healthcare provider will inject FASENRA using the single-dose prefilled syringe.
- If your healthcare provider decides that you or a caregiver can give the injection of FASENRA, you or your caregiver should receive training on the right way to prepare and give the injection using the FASENRA PEN.
- In people aged 6 to 11 years, FASENRA should only be given by a caregiver or healthcare provider.
- Do not try to inject FASENRA until you have been shown the right way by your healthcare provider. See the detailed “Instructions for Use” that comes with FASENRA PEN for information on how to prepare and inject FASENRA.
- If you miss a dose of FASENRA, call your healthcare provider.

What are the possible side effects of FASENRA?

FASENRA may cause serious side effects, including:

- allergic (hypersensitivity) reactions, including anaphylaxis. Serious allergic reactions can happen after you get your FASENRA injection. Allergic reactions can sometimes happen hours or days after you get your injection. Tell your healthcare provider or get emergency help right away if you have any of the following symptoms of an allergic reaction:
  - swelling of your face, mouth and tongue
  - breathing problems
  - fainting, dizziness, feeling lightheaded (low blood pressure)
  - rash
  - hives

The most common side effects of FASENRA include headache and sore throat.

These are not all the possible side effects of FASENRA.

Call your doctor for medical advice about side effects. You may report side effects to FDA at 1-800-FDA-1088.

How should I store FASENRA?

- Store FASENRA in the refrigerator between 36°F to 46°F (2°C to 8°C).
- FASENRA may be stored at room temperature between 68°F to 77°F (20°C to 25°C) for up to 14 days.
- Once removed from the refrigerator and brought to room temperature FASENRA must be used within 14 days or thrown away.
- Store FASENRA in the original carton until you are ready to use it to protect it from light.
- Do not freeze FASENRA. Do not use FASENRA that has been frozen.
- Do not expose FASENRA to heat.
- Do not use FASENRA past the expiration date.
- Keep FASENRA and all medicines out of the reach of children.

General information about the safe and effective use of FASENRA.

Medicines are sometimes prescribed for purposes other than those listed in a Patient Information leaflet. Do not use FASENRA for a condition for which it was not prescribed. Do not give FASENRA to other people, even if they have the same symptoms you have. It may harm them.

You can ask your doctor or pharmacist for information about FASENRA that is written for healthcare providers.

What are the ingredients in FASENRA?

Active ingredient: benralizumab

Inactive ingredients: L-histidine, L-histidine hydrochloride monohydrate, polysorbate 20, α,α-trehalose dihydrate, and Water for Injection

Manufactured by: AstraZeneca AB, Södertälje, Sweden SE-15185

U.S. License Number 2059

Distributed by: AstraZeneca Pharmaceuticals LP, Wilmington, DE 19850

FASENRA is a trademark of the AstraZeneca group of companies.

©AstraZeneca 2024

For more information, go to https://www.FASENRA.com or call 1-800-236-9933.

This Patient Information has been approved by the U.S. Food and Drug Administration. Revised: September 2024

Instructions for Use

FASENRA PEN™ (fas-en-rah)

(benralizumab)

for Subcutaneous Injection

Single-dose Autoinjector

Before using your FASENRA PEN, your healthcare provider should show you or your caregiver how to use it the right way.

In people aged 6 to 11 years, FASENRA should only be given by a caregiver or healthcare provider.

Read this Instructions for Use before you start using your FASENRA PEN and each time you get a refill. There may be new information. This information does not take the place of talking to your healthcare provider about your medical condition or your treatment.

If you or your caregiver have any questions, talk to your healthcare provider.

Important information:

- Store FASENRA in a refrigerator between 36°F to 46°F (2°C to 8°C) in its original carton until you are ready to use it.
- FASENRA may be kept at room temperature between 68°F to 77°F (20°C to 25°C) for a maximum of 14 days.
- Once removed from the refrigerator and brought to room temperature, FASENRA must be used within 14 days or thrown away (disposed of).

Do not use your FASENRA PEN if:

- it has been frozen
- it has been dropped or damaged
- the security seal on the carton has been broken
- the expiration date (EXP) has passed

Do not:

- shake your FASENRA PEN
- share or reuse your FASENRA PEN
- expose your FASENRA PEN to heat

If any of these happen, throw away the FASENRA PEN in a puncture-resistant sharps disposal container and use a new FASENRA PEN.

Each FASENRA PEN contains 1 dose of FASENRA that is for one time use only.

Keep FASENRA and all medicines out of the sight and reach of children.

Your FASENRA PEN

Do not remove the cap until you have reached Step 6 of these instructions and are ready to inject FASENRA.

Step 1 – Gather supplies

- 1 FASENRA PEN from the refrigerator
- 1 alcohol wipe
- 1 cotton ball or gauze
- 1 bandage
- 1 puncture-resistant sharps disposal container. See Step 10 for instructions on how to throw away (dispose of) the used FASENRA PEN safely.

Step 2 – Prepare to use your FASENRA PEN

Check the expiration date (EXP). Do not use if the expiration date has passed.

Let FASENRA warm up at room temperature between 68°F to 77°F (20°C to 25°C) for about 30 minutes before giving the injection.

Do not warm the FASENRA PEN in any other way. For example, do not warm it in a microwave or hot water, or put it near other heat sources.

Use FASENRA within 14 days of removing from the refrigerator. After 14 days, throw away the FASENRA PEN.

Do not remove the cap until you have reached Step 6.

Step 3 – Check the liquid

Look at the liquid in the FASENRA PEN through the viewing window. The liquid should be clear and colorless to slightly yellow. It may contain small white particles.

Do not inject FASENRA if the liquid is cloudy, discolored, or contains large particles.

You may see small air bubbles in the liquid. This is normal. You do not need to do anything about it.

Step 4 – Choose the injection site

If you are giving yourself the injection, the recommended injection site is the front of your thigh or the lower part of your stomach (abdomen).

A caregiver may inject you in the upper-arm, thigh, or abdomen. Do not try to inject yourself in the arm.

For each injection, choose a different site that is at least 1‑inch (3-cm) away from where you last injected.

Do not inject:

- into the 2-inch (5-cm) area around your bellybutton
- where the skin is tender, bruised, scaly or hard
- into scars or damaged skin
- through clothing

Step 5 – Clean the injection site

Wash your hands well with soap and water.

Clean the injection site with an alcohol wipe in a circular motion. Let it air dry.

Do not touch the cleaned area before injecting.

Do not fan or blow on the cleaned area.

Step 6 – Pull off the cap

Hold the FASENRA PEN with 1 hand. Carefully pull the cap straight off with your other hand.

Put the cap aside to throw away later.

The green needle guard is now exposed. It is there to prevent you from touching the needle.

Do not try to touch the needle or push on the needle guard with your finger.

Do not try to put the cap back on the FASENRA PEN. You could cause the

injection to happen too soon or damage the needle.

Complete the following steps right away after removing the cap.

Step 7 – Inject FASENRA

Follow your healthcare providers instructions on how to inject. You can either gently pinch at the injection site or give the injection without pinching the skin.

Inject FASENRA by following the steps in figures a, b, c, and d.

Hold the FASENRA PEN in place for the entire injection.

Do not change the position of the FASENRA PEN after the injection has started.

Position the FASENRA PEN at the injection site.

Place the needle guard of the FASENRA PEN flat against your skin (90 degree angle).

Make sure you can see the viewing window.

Press down firmly.

You will hear a click. A ‘click’ tells you the injection has started. The green plunger will move down in the viewing window during the injection.

Hold down firmly for 15 seconds.

You will hear a second ‘click’. The second click tells you the injection has finished. The green plunger will fill the viewing window.

Lift the FASENRA PEN straight up.

The needle guard will slide down and lock into place over the needle.

Step 8 – Check the viewing window

Check the viewing window to make sure all the liquid has been injected.

If the green plunger does not fill the viewing window, you may not have received the full dose. If this happens or if you have any other concerns, call your healthcare provider.

Before Injection

After Injection

Step 9 – Check the injection site

There may be a small amount of blood or liquid where you injected. This is normal.

Gently hold pressure over your skin with a cotton ball or gauze until the bleeding stops.

Do not rub the injection site.

If needed, cover the injection site with a small bandage.

Step 10 – Dispose of the used FASENRA PEN safely

- Each FASENRA PEN contains a single dose of FASENRA and cannot be reused.
- Put your used FASENRA PEN in a FDA-cleared sharps disposal container right away after use.

Do not throw away the FASENRA PEN in your household trash.

Throw away the cap and other used supplies in your household trash.

Disposal guidelines

If you do not have a FDA-cleared sharps disposal container, you may use a household container that is:

- made of a heavy-duty plastic,
- can be closed with a tight-fitting puncture-resistant lid, without sharps being able to come out,
- upright and stable during use,
- leak-resistant, and
- properly labeled to warn of hazardous waste inside the container.

When your sharps disposal container is almost full, you will need to follow your community guidelines for the right way to dispose of your sharps disposal container. There may be state or local laws about how you should throw away used needles and syringes. For more information about safe sharps disposal, and for specific information about sharps disposal in the area that you live in, go to the FDA’s website at: http://www.fda.gov/safesharpsdisposal.

Do not dispose of your used sharps disposal container in your household trash unless your community guidelines permit this.

Do not recycle your used sharps disposal container.

For more information go to www.FasenraPen.com or call 1-800-236-9933. If you still have questions, call your healthcare provider.

Manufactured by: AstraZeneca AB, Södertälje, Sweden SE-15185

U.S. License Number 2059

Distributed by: AstraZeneca Pharmaceuticals LP, Wilmington, DE 19850

FASENRA is a trademark of the AstraZeneca group of companies.

©AstraZeneca 2024

This Instructions for Use has been approved by the U.S. Food and Drug Administration

Issued: April 2024

PACKAGE/LABEL PRINCIPAL DISPLAY PANEL

NDC 0310-1730-30 Rx only

FASENRA®

(benralizumab) Injection

For Subcutaneous Injection Only

Store the prefilled syringe refrigerated at 36°F - 46°F

(2°C - 8°C) in original carton to protect from light.

Do not shake, freeze, or expose to heat.

30 mg/mL

1 single-dose prefilled syringe

Discard unused portion.

AstraZeneca

PACKAGE/LABEL PRINCIPAL DISPLAY PANEL

NDC 0310-1745-01 Rx only

FASENRA®

(benralizumab) Injection

For Subcutaneous Injection Only

Store the prefilled syringe refrigerated at 36°F - 46°F

(2°C - 8°C) in original carton to protect from light.

Do not shake, freeze, or expose to heat.

10 mg/0.5 mL

1 single-dose prefilled syringe

Discard unused portion.

AstraZeneca

Package/Label Display Panel

NDC 0310-1830-30 Rx only

FASENRA PEN™

(benralizumab) Injection

For Subcutaneous Injection Only

Store the FASENRA PEN refrigerated at 36°F - 46°F (2°C - 8°C) in original carton to protect from light.

Do not shake, freeze, or expose to heat.

30 mg/mL

1 single-dose prefilled autoinjector

Discard unused portion.

AstraZeneca